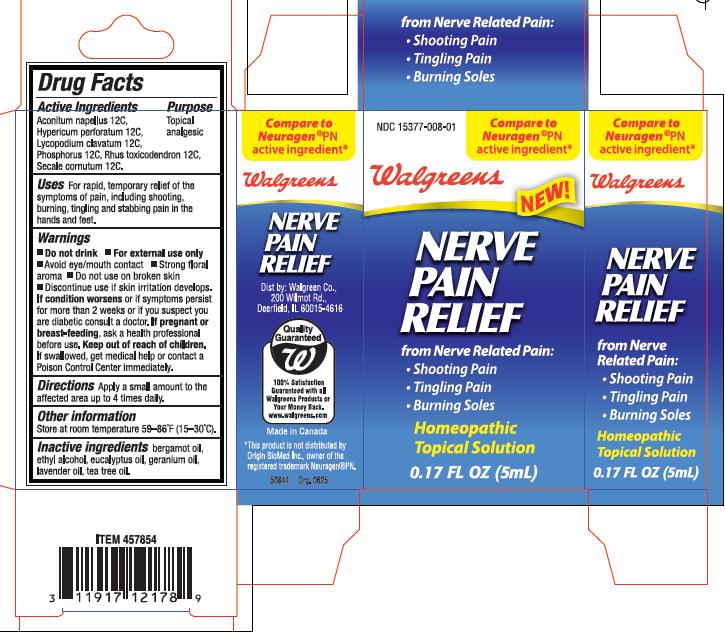 DRUG LABEL: Walgreens Nerve Pain Relief
NDC: 15377-008 | Form: SOLUTION
Manufacturer: Origin Biomed Inc.
Category: homeopathic | Type: HUMAN OTC DRUG LABEL
Date: 20100908

ACTIVE INGREDIENTS: ACONITUM NAPELLUS 12 [hp_C]/5 mL; HYPERICUM PERFORATUM 12 [hp_C]/5 mL; LYCOPODIUM CLAVATUM SPORE 12 [hp_C]/5 mL; PHOSPHORUS 12 [hp_C]/5 mL; TOXICODENDRON PUBESCENS LEAF 12 [hp_C]/5 mL; CLAVICEPS PURPUREA SCLEROTIUM 12 [hp_C]/5 mL
INACTIVE INGREDIENTS: ALCOHOL; BERGAMOT OIL; EUCALYPTUS OIL; TEA TREE OIL

PURPOSE

Topical analgesic

INDICATIONS AND USAGE

Uses: For rapid, temporary relief of the symptoms of pain, including shooting, burning, tingling and stabbing pains in the hand and feet.

WARNINGS

- Do not drink
- For external use only
- Avoid eye/mouth contact
- Strong floral aroma
- Do not use on broken skin

Discontinue use if skin irritation develops.
If condition worsens or if symptoms persist for more than 2 weeks or if you suspect you are diabetic consult a doctor.

PREGNANCY OR BREAST FEEDING

If pregnant or breast feeding, ask a health care professional before use.

Keep out of reach of children. If swallowed, get medical help or contact a Poison Control Center immediately.

DOSAGE AND ADMINISTRATION

Directions: Apply a small amount to the affected area up to 4 times daily

STORAGE AND HANDLING

Store at room temperature 59-86 degrees F (15-30 degrees C)

PACKAGE LABEL

Nerve Pain Relief

from Nerve Related Pain:

- Shooting Pain
- Tingling Pain
- Burning Soles

ACTIVE INGREDIENT

Aconitum napellus 12C, Hypericum perforatum 12C, Lycopodium clavatum 12C, Phosphorus 12C, Rhus toxicodendron 12C, Secale Cornatum 12C

INACTIVE INGREDIENT

bergamot oil, ethyl alcohol, eucalyptus oil, geranium oil, lavender oil, tea tree oil